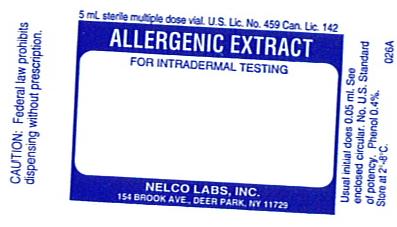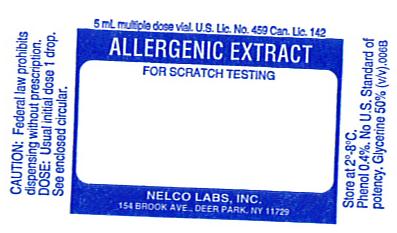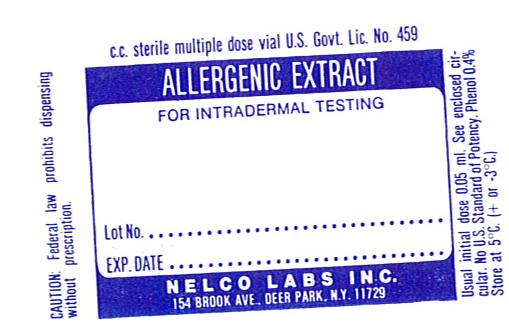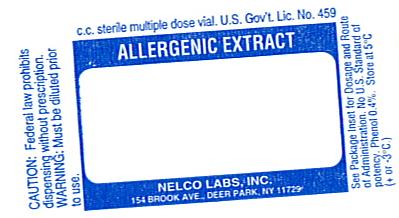 DRUG LABEL: Nigrospora sphaerica
NDC: 36987-2025 | Form: INJECTION, SOLUTION
Manufacturer: Nelco Laboratories, Inc.
Category: prescription | Type: HUMAN PRESCRIPTION DRUG LABEL
Date: 20091214

ACTIVE INGREDIENTS: KHUSKIA ORYZAE 0.05 g/1 mL
INACTIVE INGREDIENTS: SODIUM CHLORIDE; SODIUM BICARBONATE; PHENOL; WATER; GLYCERIN

Allergenic Extract

WARNING

Diagnostic and therapeutic allergenic extracts are intended to be administered by a physician who is an allergy specialist and experienced in allergenic diagnostic testing and immunotherapy and the emergency care of anaphylaxis.

This product should not be injected intravenously. Deep subcutaneous routes have been safe. Sensitive patients may experience severe anaphylactic reactions resulting in respiratory obstruction, shock, coma and/or death. (See Adverse Reactions)

Serious adverse reactions should be reported to Nelco Laboratories immediately and a report filed to: MedWatch, The FDA Medical Product Problem Reporting Program, at 5600 Fishers Lane, Rockville, Md. 20852-9787, call 1-800-FDA-1088.

Extreme caution should be taken when using allergenic extracts for patients who are taking beta-blocker medications. In the event of a serious adverse reaction associated with the use of allergenic extracts, patients receiving beta-blockers may not be responsive to epinephrine or inhaled brochodialators.(1) (See Precautions)

Allergenic extracts should be used with caution for patients with unstable or steroid-dependent asthma or underlying cardiovascular disease. (See Contraindications)

DESCRIPTION

Allergenic extracts are sterile solutions consisting of the extractable components from various biological sources including pollens, inhalants, molds, animal epidermals and insects. Aqueous extracts are prepared using cocas fluid containing NaCl 0.5%, NaHCO3 0.0275%, WFI, preservative 0.4% Phenol. Glycerinated allergenic extracts are prepared with cocas fluid and glycerin to produce a 50% (v/v) allergenic extract. Allergenic Extracts are supplied as concentrations designated as protein nitrogen units (PNU) or weight/volume (w/v) ratio. Standardized extracts are designated in Bioequivalent Allergy Units (BAU) or Allergy Units (AU). (See product insert for standardized extracts)

For diagnostic purposes, allergenic extracts are to be administered by prick-puncture or intradermal routes. Allergenic extracts are administered subcutaneously for immunotherapy injections.

CLINICAL PHARMACOLOGY

The pharmacological action of allergenic extracts used diagnostically is based on the liberation of histamine and other substances when the allergen reacts with IgE antibodies attached to the mast cells. When allergenic extracts are used for immunotherapy, the effect is an increase in immunoglobulin G (IgG) and an increased T suppresser lymphocyte which interferes with the allergic response.(2) With repeated administration of allergenic extracts changes develop in regards to IgG and IgE production and mediator-releasing cells. The histamine release response is reduced in some patients.

INDICATIONS AND USAGE

Allergenic extracts are indicated for use in diagnostic testing and as part of a treatment regime for allergic disease, as established by allergy history and skin test reactivity.

Allergenic extracts are indicated for the treatment of allergen specific allergic disease for use as hyposensitization or immunotherapy when avoidance of specific allergens can not be attained. The use of allergenic extracts for therapeutic purpose has been established by well-controlled clinical studies. Allergenic extracts may be used as adjunctive therapy along with pharmacotherapy which includes antihistamines, corticosteroids, and cromoglycate, and avoidance measures. Allergenic extracts for therapeutic use should be given using only the allergen selection to which the patient is allergic, has a history of exposure and are likely to be exposed to again.

CONTRAINDICATIONS

Allergenic extracts should not be used if the patient has asthma, cardiovascular disease, emphysema, diabetes, bleeding diathesis or pregnancy, unless a specific diagnosis of type 1 allergic disease is made based on skin testing and the benefits of treatment outweigh the risks of an adverse reaction during testing or treatment. Allergenic extracts are not indicated for use in patients who are not clinically allergic or who are not skin reactive to an allergen. Allergenic extracts should be discontinued or the concentration of potency substantially reduced in patients who experience unacceptable adverse reactions.

WARNINGS

DO NOT INJECT INTRAVENOUSLY.

Epinephrine 1:1000 should be available.

Concentrated extracts must be diluted with sterile diluent prior to first use on a patient for treatment or intradermal testing. All concentrates of glycerinated allergenic extracts have the ability to cause serious local and systemic reactions including death in sensitive patients. Sensitive patients may experience severe anaphylactic reactions resulting in respiratory obstruction, shock, coma and /or death.(4) (See Adverse Reactions) An allergenic extract should be temporarily withheld from patients or the dose of the extract adjusted downward if any of the following conditions exist: (1) Severe symptoms of rhinitis and/or asthma (2) Infections or flu accompanied by fever and (3) Exposure to excessive amounts of clinically relevant allergen prior to a scheduled injection. When switching patients to a new lot of the same extract the initial dose should be reduced 3/4 so that 25% of previous dose is administered.

PRECAUTIONS

GENERAL: Epinephrine 1:1000 should be available as well as personnel trained in administering emergency treatment. Allergenic Extracts are not intended for intravenous injections. For safe and effective use of allergenic extracts, sterile diluents, sterile vials, sterile syringes should be used and aseptic precautions observed when making a dilution and/or administering the allergenic extract injection. A sterile tuberculin syringe graduated in 0.1 ml units to measure each dose for the prescribed dilution should be used. To reduce the risk of an occurrence of adverse reactions, begin with a careful personal history plus a physical exam. Confirm your findings with scratch or intradermal skin testing.

Standardized extracts are those labeled in AU/ml units or BAU/ml units. Standardized extracts are not interchangeable with extracts previously labeled as wt/vol or PNU/ml. Before administering a standardized extract, read the accompanying insert contained with standardized extracts.

Information for Patients: All concentrates of allergenic extracts have the ability to cause serious local and systemic reactions including death in sensitive patients. Patients should be informed of this risk prior to skin testing and immunotherapy. Patients should be instructed to recognize adverse reaction symptoms that may occur and to report all adverse reactions to a physician. Patients should be instructed to remain in the office for 30 minutes during testing using allergenic extracts and at least 30 minutes after therapeutic injections using allergenic extracts.

DRUG INTERACTIONS: Some drugs may affect the reactivity of the skin; patients should be instructed to avoid medications, particularly antihistamines and sympathomimetic drugs, for at least 24 hours prior to skin testing. Antihistamines and Hydroxyzine can significantly inhibit the immediate skin test reactions as they tend to neutralize or antagonize the action of histamine.(3) This effect has been primarily documented when testing was performed within 1 to 2 hours after drug ingestion. Partial inhibition of the skin test reaction had been observed for longer periods. Epinephrine injection inhibits the immediate skin test reactions for several hours. Patients on delayed absorption antihistamine tablets should be free of such medication for 48 hours before testing. Patients using Astemizole (Hismanal) may experience prolonged suppression and should be free from such medication for up to 6 to 8 weeks prior to testing. Refer to package insert from an applicable long acting antihistamine manufacturer for additional information.

Extreme caution should be taken when using allergenic extracts on patients who are taking beta-blockers. Patients on non-selective beta blockers may be more reactive to allergens given for testing or treatment and may be unresponsive to the usual doses of epinephrine used to treat allergic reactions.

Carcinogenesis, mutagenesis, impairment of fertility:

Long term studies in animals have not been conducted with allergenic extracts to determine their potential carcinogenicity, mutagenicity or impairment of fertility.

Pregnancy: Category C: Animal reproduction studies have not been conducted with Allergenic Extracts. It is not known whether allergenic extracts can cause fetal harm when administered to pregnant women or can affect reproduction capacity. Allergenic extracts should be given to pregnant women only if clearly needed.

Nursing Mothers: It is not known whether this drug appears in human milk. Because many drugs are detected in human milk, caution should be exercised when Allergenic Extracts are administered to a nursing woman. There are no current studies on extract components in human milk, or their effect on the nursing infant.

Pediatric Use: Allergenic extracts have been used in children over two years of age.(5)

ADVERSE REACTIONS

Adverse systemic reactions usually occur within minutes and consist primarily of allergic symptoms such as: generalized skin erythema, urticaria, pruritus, angioedema, rhinitis, wheezing, laryngeal edema, itching of nose and throat, breathlessness, dyspnea, coughing, hypotension and marked perspiration. Less commonly, nausea, emesis, abdominal cramps, diarrhea and uterine contractions may occur. Severe reactions may cause anaphylaxis or shock and loss of consciousness and rarely death.

The treatment of systemic allergic reactions is dependent upon the system complex. Antihistamines may offer relief of recurrent urticaria, associated skin reactions and gastrointestinal symptoms. Corticosteroids may provide benefit if symptoms are prolonged or recurrent. (See Overdose section)

Local Reactions consisting of erythema, itching, swelling tenderness and sometimes pain may occur at the injection site. These reactions may appear within a few minutes to hours and persist for several days. Local cold applications and oral antihistamines may be effective treatment. For marked and prolonged local reactions the use of antihistamines or anti-inflammatory medications may be dictated. Serious adverse reactions should be reported to Nelco Laboratories immediately and a report can be filed to: MedWatch, The FDA Medical Product Problem Reporting Program, at 5600 Fishers Lane, Rockville, MD 20852-9787, call 1-800-FDA-1088.

OVERDOSAGE

Overdose can cause both local and systemic reactions. An overdose may be prevented by careful observation and questioning of the patient about the previous injection.

If systemic or anaphylactic reaction, does occur, apply a tourniquet above the site of injection and inject intramuscularly or subcutaneously 0.3 to 0.5ml of 1:1000 Epinephrine Hydrochloride into the opposite arm. The dose may be repeated in 5-10 minutes if necessary. Loosen the tourniquet at least every 10 minutes. The Epinephrine Hydrochloride 1:1000 dose for infants to 2 years is 0.1 to 0.1 ml, for children 2 to 6 years it is 0.15 ml, for children 6-12 years it is 0.2 ml.

Patients unresponsive to Epinephrine may be treated with Theophylline. Studies on asthmatic subjects reveal that plasma concentrations of Theophylline of 5 to 20 µg/ml are associated with therapeutic effects. Toxicity is particularly apparent at concentrations greater than 20 µg/ml. A loading dose of Aminophylline of 5.8 mg/kg intravenously followed by 0.9 mg/kg per hour results in plasma concentrations of approximately 10 µg/ml for patients not previously receiving theophylline. (Mitenko and Ogilive, Nicholoson and Chick,1973)

Other beta-adrenergic drugs such as Isoproterenol, Isoetharine, or Albuterol may be used by inhalation. The usual dose to relieve broncho-constriction in asthma is 0.5 ml of the 0.5% solution for Isoproterenol HCl. The Albuterol inhaler delivers approximately 90 mcg of Albuterol from the mouthpiece. The usual dosage for adults and children would be two inhalations repeated every 4-6 hours. Isoetharine supplied in the Bronkometer unit delivers approximately 340 mcg Isoetharine. The average dose is one to two inhalations. Respiratory obstruction not responding to parenteral or inhaled bronchodilators may require oxygen, intubation and the use of life support systems.

DOSAGE AND ADMINISTRATION

General Precautions

Parenteral drug products should be inspected visually for particulate matter and discoloration prior to administration whenever solution and container permits.

The dosage of allergenic extracts is dependent upon the purpose of the administration. Allergenic extracts can be administered for diagnostic use or for therapeutic use.

When allergenic extracts are administered for diagnostic use, the dosage is dependent upon the method used. Two methods commonly used are scratch testing and intradermal testing. Both types of tests result in a wheal and flare response at the site of the test which usually develops rapidly and may be read in 20-30 minutes.

Diagnostic Use: Scratch Testing Method

Scratch testing is considered a simple and safe method although less sensitive than the intradermal test. Scratch testing can be used to determine the degree of sensitivity to a suspected allergen before using the intradermal test. This combination lessens the severity of response to an allergen which can occur in a very sensitive patient.

The most satisfactory testing site is the patient's back or volar surface of the arms from the axilla to 2.5 or 5cm above the wrist, skipping the anti-cubital space. If using the back as a testing site, the most satisfactory area are from the posterior axillary fold to 2.5 cm from the spinal column, and from the top of the scapula to the lower rib margins.

Allergenic extracts for diagnostic use are to be administered in the following manner: To scratch surface of skin, use a circular scarifier. Do not draw blood. Tests sites should be 4 cm apart to allow for wheal and flare reaction. 1-30 scratch tests may be done at a time. A separate sterile scratch instrument is to be used on each patient to prevent transmission of homologous serum hepatitis or other infectious agents from one patient to another.

The recommended usual dosage for Scratch testing is one drop of allergen applied to each scratch site. Do not let dropper touch skin. Always apply a control scratch with each test set. Sterile Diluent (for a negative control) is used in exactly the same way as an active test extract. Histamine may be used as a positive control. Scratch or prick test sites should be examined at 15 and 30 minutes. To prevent excessive absorption, wipe off antigens producing large reactions as soon as the wheal appears. Record the size of the reaction.

Interpretation of Scratch Test

Skin tests are graded in terms of the wheal and erythema response noted at 10 to 20 minutes. Wheal and erythema size may be recorded by actual measurement as compared with positive and negative controls. A positive reaction consists of an area of erythema surrounding the scarification that is larger than the control site. For uniformity in reporting reactions, the following system is recommended. (6)

REACTION | SYMBOL | CRITERIA
Negative | - | No wheal. Erythema absent or very slight (not more than 1 mm diameter).
One Plus | + | Wheal absent or very slight erythema present (not more than 3 mm diameter).
Two Plus | ++ | Wheal not more than 3mm or erythema not more than 5mm diameter.
Three Plus | +++ | Wheal between 3mm and 5mm diameter, with erythema. Possible pseudopodia and itching.
Four Plus | ++++ | A larger reaction with itching and pain.

Diagnostic Use: Intradermal Skin Testing Method

Do not perform intradermal test with allergens which have evoked a 2+ or greater response to a Scratch test. Clean test area with alcohol, place sites 5 cm apart using separate sterile tuberculin syringe and a 25 gauge needle for each allergen. Insert needle tip, bevel up, into intracutaneous space. Avoid injecting into blood vessel, pull back gently on syringe plunger, if blood enters syringe change position of needle. The recommended dosage and range for intradermal testing is 0.1 ml of not more than 100 pnu/ml or 1:1000 w/v (only if puncture test is negative) of allergenic extract. Inject slowly until a small bleb is raised. It is important to make each bleb the same size.

Interpretation of Intradermal Test:

The patient's reaction is graded on the basis of size of wheal and flare as compared to control. Use 0.1 ml sterile diluent as a negative control to give accurate interpretation. The tests may be accurately interpreted only when the saline control site has shown a negative response. Observe patient for at least 30 minutes. Tests can be read in 15-20 minutes. Edema, erythema and presence of pseudopods, pain and itching may be observed in 4 plus reactions. For uniformity in reporting reactions the following system is recommended. (6)

REACTION | SYMBOL | CRITERIA
Negative | - | No increase in size of bleb since injection. No erythema.
One Plus | + | An increase in size of bleb to a wheal not more than 5mm diameter, with associated erythema.
Two Plus | ++ | Wheal between 5mm and 8mm diameter with erythema.
Three Plus | +++ | Wheal between 8mm and 12mm diameter with erythema and possible pseudopodia and itching or pain.
Four Plus | ++++ | Any larger reaction with itch and pain, and possible diffuse blush of the skin surrounding the reaction area.

Therapeutic Use: Recommended dosage & range

Check the listed ingredients to verify that it matches the prescription ordered. When using a prescription set, verify the patient's name and the ingredients listed with the prescription order. Assess the patient's physical and emotional status prior to giving as injection. Do not give injections to patients who are in acute distress. Parenteral drug products should be inspected visually for particulate matter and discoloration prior to administration, whenever solution and container permit.

Dosage of allergenic extracts is a highly individualized matter and varies according to the degree of sensitivity of the patient, his clinical response and tolerance to the extract administered during the early phases of an injection regimen. The dosage must be reduced when transferring a patient from non-standardized or modified extract to standardized extract. Any evidence of a local or generalized reaction requires a reduction in dosage during the initial stages of immunotherapy as well as during maintenance therapy. After therapeutic injections patients should be observed for at least 20 minutes for reaction symptoms.

SUGGESTED DOSAGE SCHEDULE

The following schedule may act as a guide. This schedule has not been proven to be safe or effective. Sensitive patients may begin with smaller doses of weaker solutions and the dosage increments can be less.

STRENGTH | DOSE | VOLUME
Vial #1 | 1 | 0.1
1:100,000 w/v | 2 | 0.10
10 pnu/ml | 3 | 0.15
1 AU/ml | 4 | 0.20
1 BAU/ml | 5 | 0.30
 | 6 | 0.40
 | 7 | 0.50
Vial #2 | 8 | 0.1
1:10,000 w/v | 9 | 0.10
100 pnu/ml | 10 | 0.15
10 AU/ml | 11 | 0.20
10 BAU/ml | 12 | 0.30
 | 13 | 0.40
 | 14 | 0.50
Vial #3 | 15 | 0.1
1:1,000 w/v | 16 | 0.10
1,000 pnu/ml | 17 | 0.15
100 AU/ml | 18 | 0.20
100 BAU/ml | 19 | 0.30
 | 20 | 0.40
 | 21 | 0.50
Vial #4 | 22 | 0.1
1:100 w/v | 23 | 0.07
10,000 pnu/ml | 24 | 0.10
1,000 AU/ml | 25 | 0.15
1,000 BAU/ml | 26 | 0.20
 | 27 | 0.25
Maintenance Refill | 28 | 0.25
1:100 w/v | 29 | 0.25
10,000 pnu/ml | 30 | 0.25
1,000 AU/ml | 31 | 0.25
1,000 BAU/ml | 32 | 0.25
subsequent doses | 33 | 0.25

Preparation Instructions:

All dilutions may be made using sterile buffered diluent. The calculation may be based on the following ratio:

Volume desired x Concentration desired = Volume needed x Concentration available.

Example 1: If a 1:10 w/v extract is available and it is desired to use a 1:1,000 w/v extract substitute as follows:

Vd x Cd = Vn x Ca

10ml x 0.001 = Vn x 0.1

0.1 ml = Vn

Using a sterile technique, remove 0.10 ml of extract from the 1:10 vial and place it into a vial containing 9.90 ml of sterile diluent. The resulting ratio will be a 10 ml vial of 1:1,000 w/v.

Example 2: If a 10,000 pnu/ml extract is available and it is desired to use a 100 pnu/ml extract substitute as follows:

10ml x 100 = Vn x 10,000

0.1 ml = Vn

Using a sterile technique, remove 0.10 ml of extract from the 10,000 pnu/ml vial and place it into a vial containing 9.90 ml of sterile diluent. The resulting concentration will be a 10 ml vial of 100 pnu/ml.

Example 3: If a 10,000 AU/ml or BAU/ml extract is available and it is desired to use a 100 AU/ml or BAU/ml extract substitute as follows: Vd x Cd = Vn x Ca

10ml x 100 = Vn x 10,000

0.1 ml = Vn

Using a sterile technique, remove 0.10 ml of extract from the 10,000 AU/ml or BAU/ml vial and place it into a vial containing 9.90 ml of sterile diluent. The resulting concentration will be 10ml vial of 100 AU/ml or BAU/ml.

Intervals between doses: The optimal interval between doses of allergenic extract has not been definitely established. The amount of allergenic extract is increased at each injection by not more than 50%-100% of the previous amount and the next increment is governed by the response to the last injection. There are three generally accepted methods of pollen hyposensitizing therapy.

1. PRESEASONAL

Treatment starts each year 6 to 8 weeks before onset of seasonal symptoms. Maximal dose reached just before symptoms are expected. Injections discontinued during and following season until next year.

2. CO-SEASONAL

Patient is first treated during season with symptoms. Low initial doses are employed to prevent worsening of condition. This is followed by an intensive schedule of therapy (i.e. injections given 2 to 3 times per week). Fewer Allergists are resorting to this Co-seasonal therapy because of the availability of more effective, symptomatic medications that allow the patient to go through a season relatively symptom free.

3. PERENNIAL

Initially this is the same as pre seasonal. The allergen is administered twice weekly or weekly for about 20 injections to achieve the maximum tolerated dose. Then, maintenance therapy may be administered once a week or less frequently.

Duration of Treatment: The usual duration of treatment has not been established. A period of two or three years of injection therapy constitutes an average minimum course of treatment.

HOW SUPPLIED

Allergenic extracts are supplied with units listed as: Weight/volume (W/V), Protein Nitrogen Units (PNU/ml), Allergy Units (AU/ml) or Bioequivalent Allergy Units (BAU/ml).

Sizes:

Diagnostic Scratch: 5 ml dropper application vials

Diagnostic Intradermal: 5 ml or 10 ml vials.

Therapeutic Allergens: 5 ml, 10 ml, 50 ml multiple dose vials.

STORAGE

The expiration date of allergen extracts is listed on the container label. Store extracts upon arrival at 2° to 8°C and keep them in this range during office use.

WARRANTY: We warrant that this product was prepared and tested according to the standards of the FDA and is true to label. Because of biological differences in individuals and because allergenic extracts are manufactured to be potent and because we have no control over the conditions of use, we cannot and do not warrant either a good effect or against an ill effect following use.

REFERENCES

1 Jacobs, Robert L., Geoffrey W.Rake,Jr., et.al. Potentiated Anaphylaxis in Patients with Drug-induced Beta-adrenergic Blockade. J.Allergy & Clin. Immunol., 68(2): 125-127. August 1981.

2 Ishizaka,K.: Cellular Events in the IgE Antibody Response. Adv. in Immuno. 23:50-75, 1976.

3. Lockey, R.F., Bukantz, S.C., Allergen Immunotherapy. New York,NY: Marcel Dekker Inc., 1991.

4. Reid,M.J., Lockey,R.F., Turkeltaub,P.C., Platts-Mills,T.A.E., Survey of fatalities from skin testing and immunotherapy 1985-1989. Journal of Allergy Clin. Immunol. 92 (1): 6-15, July 1993.

5. Murray, A.B., Ferguson, A., Morrison, B., The frequency and severity of cat allergy vs dog allergy in atopic children. J. Allergy Clin. Immunolo: 72, 145-9, 1985.

6. Lockey, R.F., Bukantz, S.C., Allergen Immunotherapy. New York,NY: Marcel Dekker Inc., 1991.